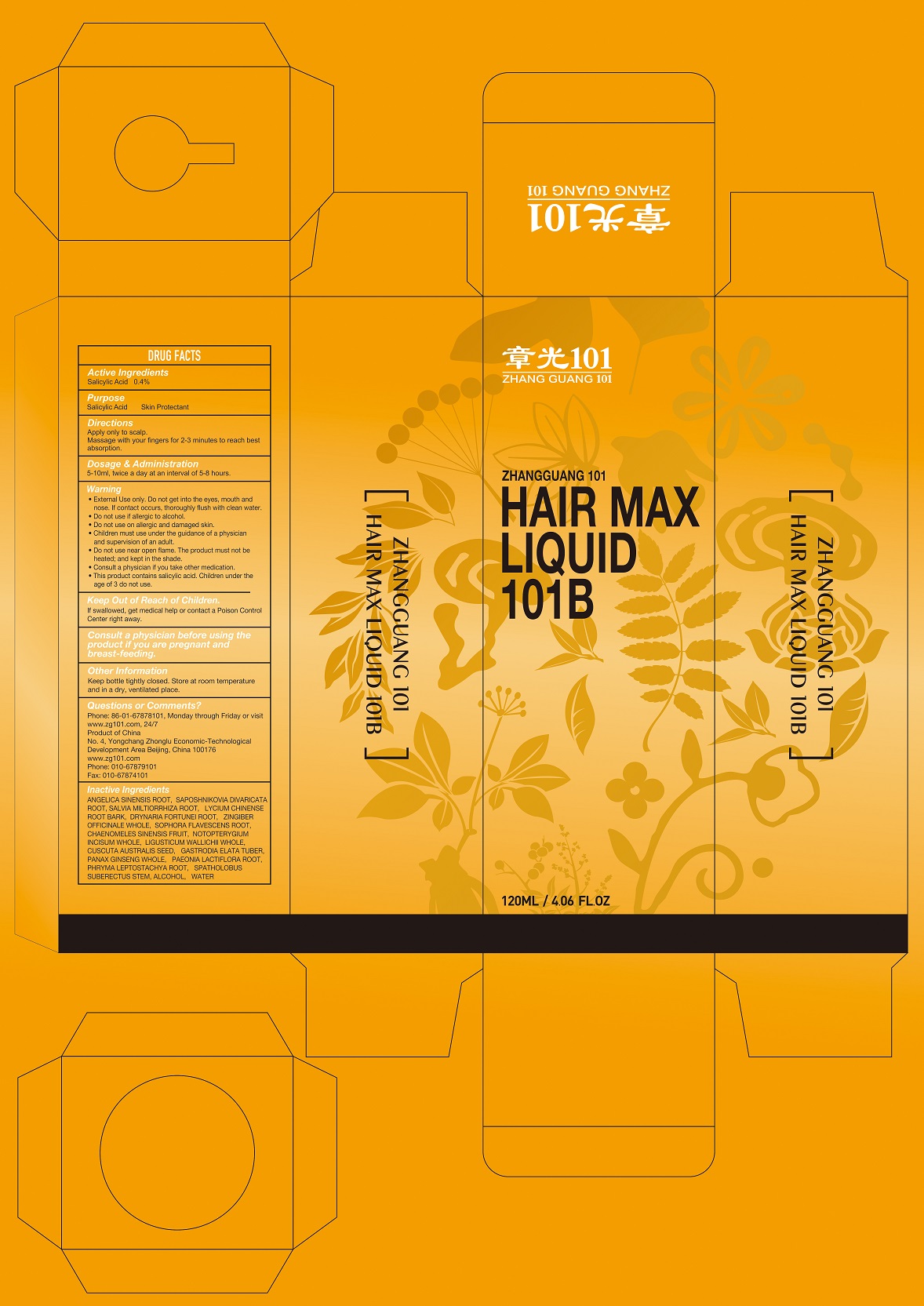 DRUG LABEL: ZHANGGUANG 101 HAIR MAX 101B
NDC: 71675-004 | Form: LIQUID
Manufacturer: Beijing Zhangguang 101 Science and Technology Co Ltd
Category: otc | Type: HUMAN OTC DRUG LABEL
Date: 20211223

ACTIVE INGREDIENTS: SALICYLIC ACID 0.4 g/100 mL
INACTIVE INGREDIENTS: ANGELICA SINENSIS ROOT; SAPOSHNIKOVIA DIVARICATA ROOT; SALVIA MILTIORRHIZA ROOT; LYCIUM CHINENSE ROOT BARK; DRYNARIA FORTUNEI ROOT; ZINGIBER OFFICINALE WHOLE; SOPHORA FLAVESCENS ROOT; CHAENOMELES SINENSIS FRUIT; NOTOPTERYGIUM INCISUM WHOLE; LIGUSTICUM WALLICHII WHOLE; CUSCUTA AUSTRALIS SEED; GASTRODIA ELATA TUBER; PANAX GINSENG WHOLE; PAEONIA LACTIFLORA ROOT; PHRYMA LEPTOSTACHYA ROOT; SPATHOLOBUS SUBERECTUS STEM; ALCOHOL; WATER

Beijing Zhangguang 101 Science & Technology Co, Ltd

Active Ingredients

Salicylic Acid 0.4%

Purpose

Salicylic Acid Skin Protectant

Directions

Apply only to scalp.
Massage with your fingers for 2-3 minutes to reach best absorption.

Dosage & Administration

5-10ml, twice a day at an interval of 5-8 hours.

Warning

• External Use only. Do not get into the eyes, mouth and nose. If contact occurs, thoroughly flush with clean water.
• Do not use if allergic to alcohol.
• Do not use on allergic and damaged skin.
• Children must use under the guidance of a physician and supervision of an adult.
• Do not use near open flame. The product must not be heated; and kept in the shade.
• Consult a physician if you take other medication.
• This product contains salicylic acid. Children under the age of 3 do not use.

Keep Out of Reach of Children.

If swallowed, get medical help or contact a Poison Control Center right away.

Other Information

Keep bottle tightly closed. Store at room temperature and in a dry, ventilated place.

Questions or Comments?

Phone: 86-01-67878101, Monday through Friday or visit www.zg101.com, 24/7
Product of China
No. 4, Yongchang Zhonglu Economic-Technological Development Area Beijing, China 100176
www.zg101.com
Phone: 010-67879101
Fax: 010-67874101

Inactive Ingredients

ANGELICA SINENSIS ROOT, SAPOSHNIKOVIA DIVARICATA ROOT, SALVIA MILTIORRHIZA ROOT, LYCIUM CHINENSE ROOT BARK, DRYNARIA FORTUNEI ROOT, ZINGIBER OFFICINALE WHOLE, SOPHORA FLAVESCENS ROOT, CHAENOMELES SINENSIS FRUIT, NOTOPTERYGIUM INCISUM WHOLE, LIGUSTICUM WALLICHII WHOLE, CUSCUTA AUSTRALIS SEED, GASTRODIA ELATA TUBER, PANAX GINSENG WHOLE, PAEONIA LACTIFLORA ROOT, PHRYMA LEPTOSTACHYA ROOT, SPATHOLOBUS SUBERECTUS STEM, ALCOHOL, WATER